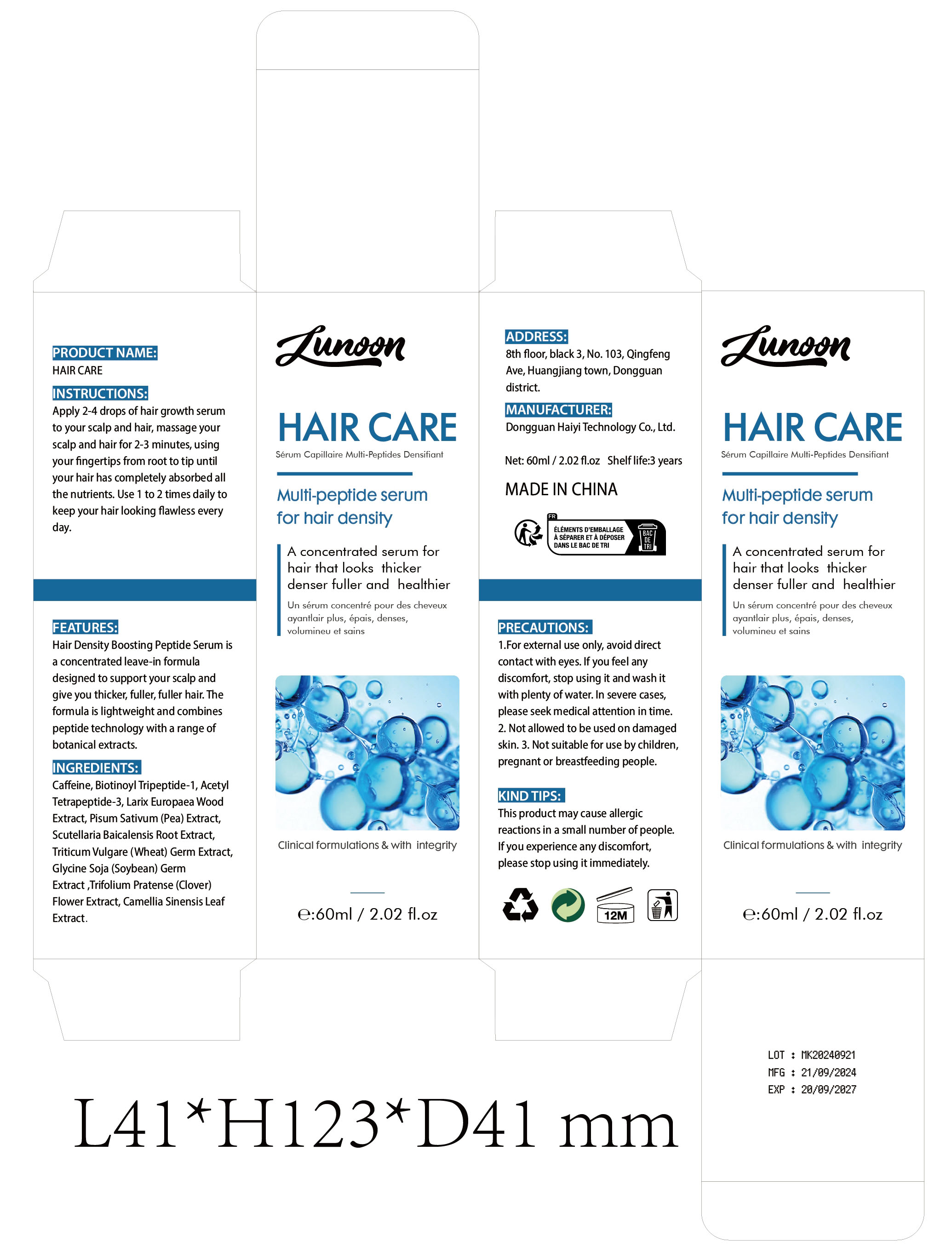 DRUG LABEL: HAIR CARE
NDC: 84732-037 | Form: LIQUID
Manufacturer: Dongguan Haiyi Technology Co.,Ltd.
Category: otc | Type: HUMAN OTC DRUG LABEL
Date: 20241009

ACTIVE INGREDIENTS: CAFFEINE 1 mg/100 mL
INACTIVE INGREDIENTS: WHEAT GERM; TRIFOLIUM PRATENSE FLOWER; BIOTINOYL TRIPEPTIDE-1; LARIX DECIDUA WOOD; PEA; ACETYL TETRAPEPTIDE-3; SCUTELLARIA BAICALENSIS ROOT; GREEN TEA LEAF

Active ingredient

Caffeine

Inactive ingredient

Biotinoyl Tripeptide-1, Acetyl Tetrapeptide-3, Larix Europaea Wood Extract, Pisum Sativum (Pea) Extract,Scutellaria Baicalensis Root Extract,Triticum Vulgare (Wheat) Germ Extract,Glycine Soja (Soybean) Germ Extract ,Trifolium Pratense (Clover) Flower Extract, Camellia Sinensis Leaf Extract.

Purpose section

Hair Density Boosting Peptide Serum is a concentrated leave-in formula designed to support your scalp and give you thicker, fuller, fuller hair. The formula is lightweight and combine speptide technology with a range of botanical extracts.

Warning

1.For external use only, avoid directcontact with eyes. lf you feel anydiscomfort, stop using it and wash itwith plenty of water. In severe casesplease seek medical attention in time.

2. Not allowed to be used on damagedskin.

3. Not suitable for use by children,pregnant or breast feeding people.

stop use

This product may cause allergic reactions in asmall number of people.
lf youexperience any discomfort,please stop using it immediately.

not use

Not suitable for use by children, pregnantor breast feeding people.

OUT OF CHILDREN

KEEP THE PRODUCT OUT OF REACH OF CHILDREN to

HOW TO USE

Apply 2-4 drops of hair growth serum to your scalp and hair, massage your scalp and hair for 2-3 minutes, usingyour fnger tips from root to tip until your hair has completely absorbed all the nutrients. Use 1 to 2 times daily to keep your hair looking flawless everyday.

Dosage

take an appropriateamount,Use 2-3 times a week